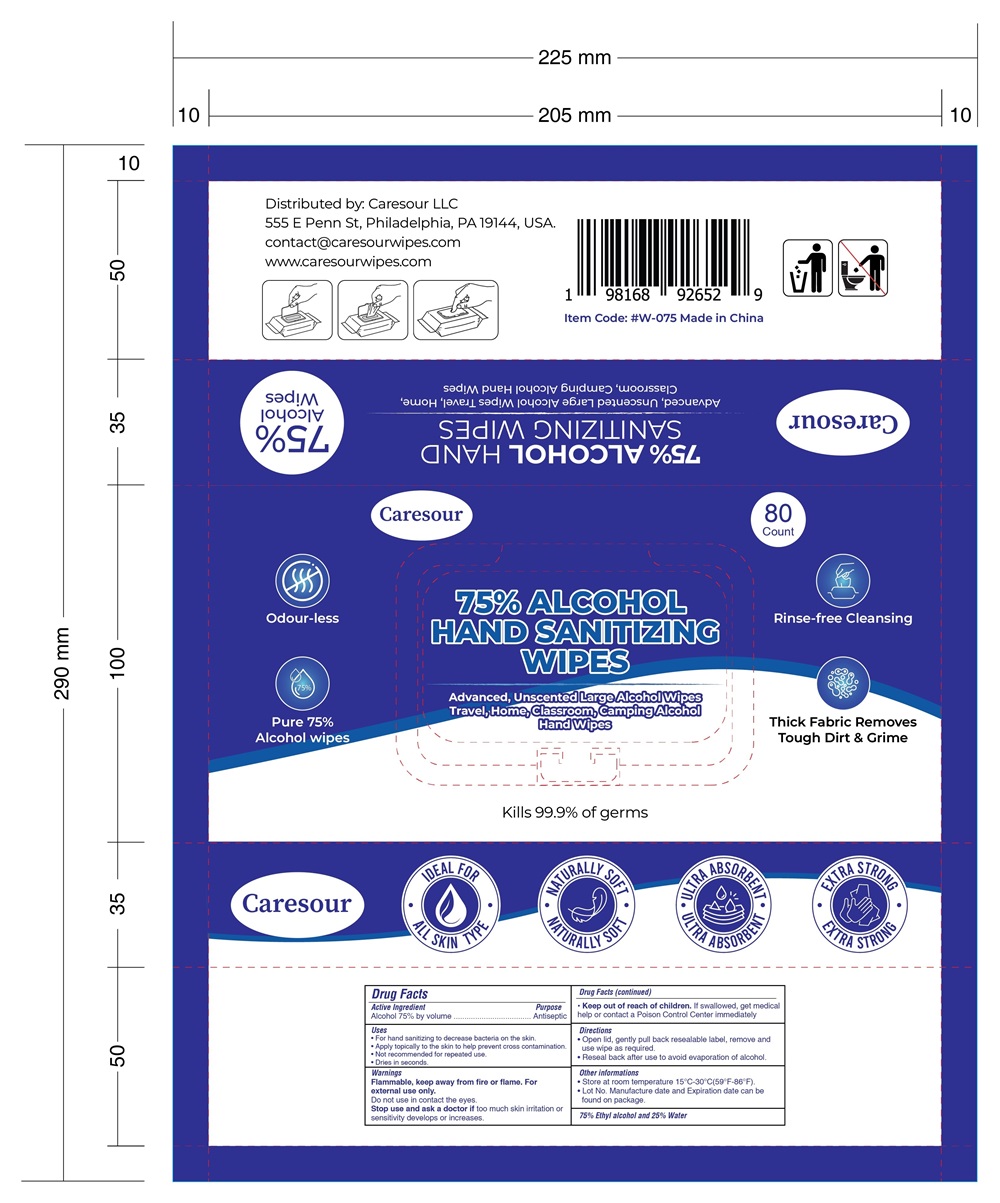 DRUG LABEL: Caresour Alcohol Wipes
NDC: 52489-004 | Form: CLOTH
Manufacturer: Imperial Palace Commodity(Shenzhen)CO.,LTD
Category: otc | Type: HUMAN OTC DRUG LABEL
Date: 20240926

ACTIVE INGREDIENTS: ALCOHOL 591 mg/1 mL
INACTIVE INGREDIENTS: WATER; GLYCERIN

ACTIVE INGREDIENT

Alcohol 75%

PURPOSE

Cleaning and disinfection

Uses

Packs

Peel back lid and then label.
Remove wipes as required.
Replace lid and label to keep wipes moist.

Buckets

Open the bucket lid from the top.
Locate tear cut in the inner pouch, tear straight to open. Do not remove wipesroll from pouch.
Pull first wipes from center of roll up through opening.
Thread first wipe through dispensing nozzle in top of roll.
Close the bucket lid and dispense the wipes as required.

WARNINGS

For external use only.
Store in cool and dry place.keep away from heat and direct sunlight.
Avoid touching eyes. In case of eye contact, flush thoroughly with water.
Avoid contact with broken skin.
Don't flush into toilet.
Stop use and ask a doctor if skin irritation develops.

In case of accidental ingestion, seekprofessional assistance or contact a Poison Control Center immediately.

DOSAGE AND ADMINISTRATION

Thoroughly moisten the skin or solid surface with the product and let it dry without wiping
For children under 6, use only under adult supervision.
Not recommended for infants.

INACTIVE INGREDIENT

Water, Glycerin

Keep out of reach of children.